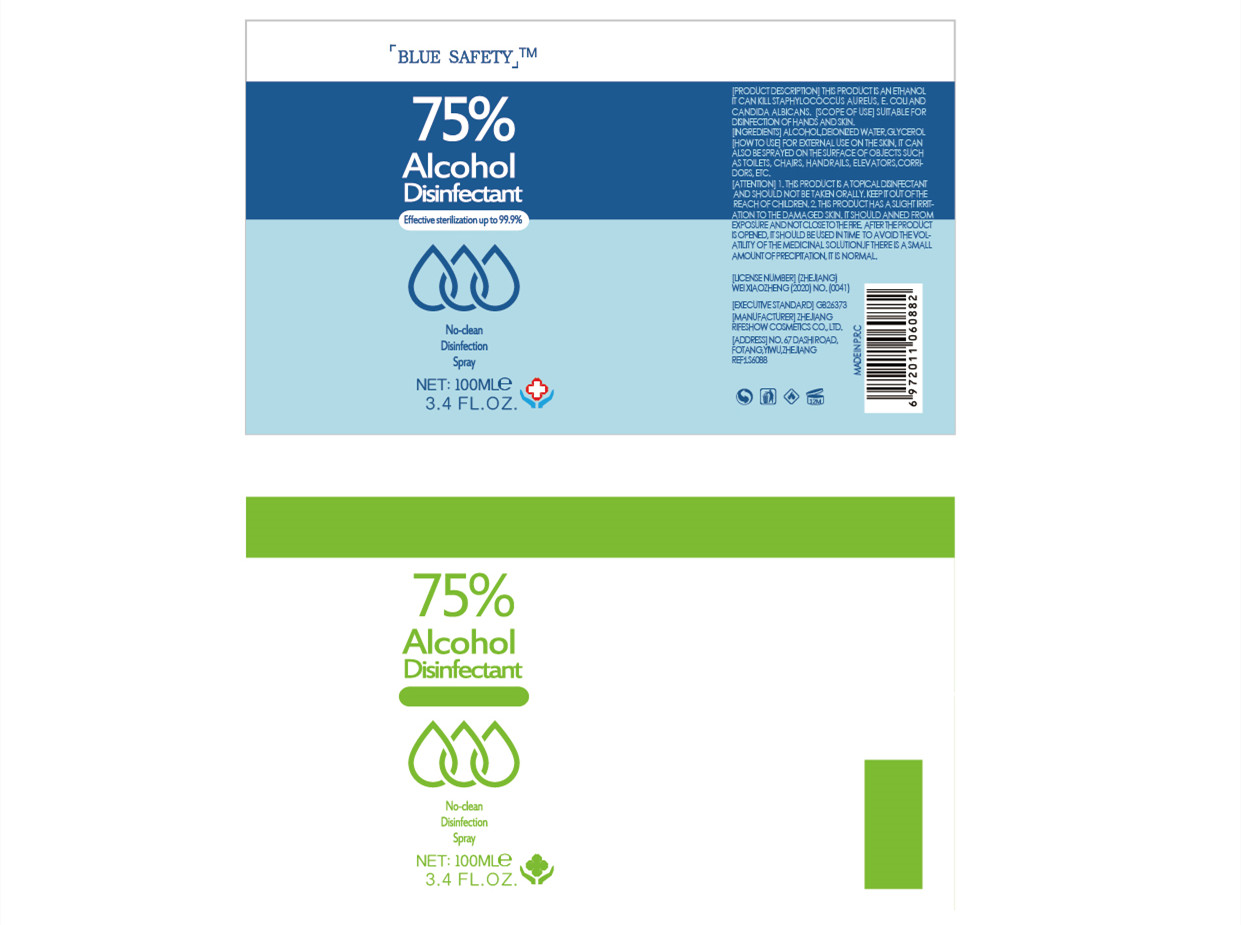 DRUG LABEL: 75%Alcohol disinfectant
NDC: 56084-014 | Form: LIQUID
Manufacturer: ZHEJIANG RIFESHOW COSMETICS CO.,LTD
Category: otc | Type: HUMAN OTC DRUG LABEL
Date: 20200512

ACTIVE INGREDIENTS: ALCOHOL 73.5 mL/100 mL
INACTIVE INGREDIENTS: WATER

ACTIVE INGREDIENT

Alcohol

INACTIVE INGREDIENT

Deionized water

PURPOSE

Eflective serilizationupo99.9%

WARNINGS

1.IHS PRODUCT I ATOPICALDENECTANT AND SHOULD NOT BE TAKEN ORALLY. KEEP IT OUT OF THE REACHOF CHLDREN
2 THS PROOUCTHAS ASUIGH RIT-ATION TO THE DAMAGED SKIN ITSHOULD ANNED FROM EXPOSURE AND NOT CLOSE TO THE FIRE

keep out of children

DOSAGE AND ADMINISTRATION

Not close to the fire.

INDICATIONS AND USAGE

Disinfection
Sterilization